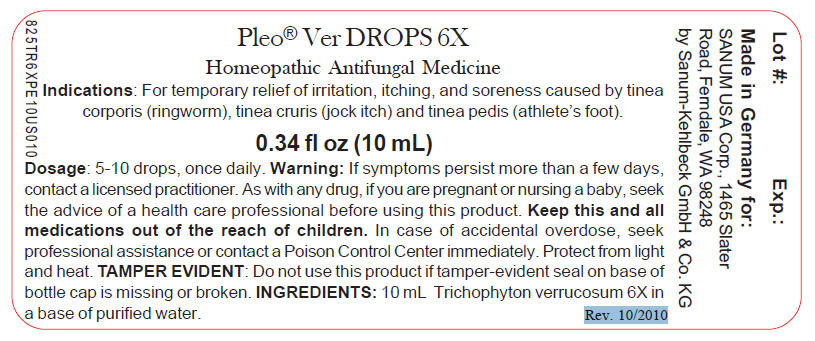 DRUG LABEL: Pleo Ver
NDC: 60681-5701 | Form: SOLUTION/ DROPS
Manufacturer: SANUM-KEHLBECK GMBH & CO KG
Category: otc | Type: HUMAN OTC DRUG LABEL
Date: 20110128

ACTIVE INGREDIENTS: Trichophyton Verrucosum 6 [hp_X]/10 mL
INACTIVE INGREDIENTS: water

Pleo® Ver
DROPS 6X

PURPOSE

Homeopathic Antifungal Medicine

0.34 fl oz
(10 mL)

Indications

For temporary relief of irritation, itching, and soreness caused by tinea corporis (ringworm), tinea cruris (jock itch) and tinea pedis (athlete's foot).

DOSAGE

5-10 drops, once daily.

WARNING

If symptoms persist more than a few days, contact a licensed practitioner.

PREGNANCY OR BREAST FEEDING

As with any drug, if you are pregnant or nursing a baby, seek the advice of a health care professional before using this product.

KEEP OUT OF REACH OF CHILDREN

Keep this and all other medications out of the reach of children. In case of accidental overdose, seek professional assistance or contact a Poison Control Center immediately.

STORAGE AND HANDLING

Protect from light and heat.

INGREDIENTS

INACTIVE INGREDIENT

10 mL Trichophyton verrucosum 6X in a base of purified water.

Tamper Evident

Do not use this product if tamper-evident seal on base of bottle cap is missing or broken.

Made in Germany

Distributed by:
SANUM USA Corp.
1465 Slater Road
Ferndale, WA 98248

Manufactured by:
Sanum-Kehlbeck
GmbH & Co. KG
Hoya, Germany

Rev. 10/2010

PRINCIPAL DISPLAY PANEL - 10 mL Bottle Label

Pleo® Ver DROPS 6X

Homeopathic Antifungal Medicine

Indications: For temporary relief of irritation, itching, and soreness caused by tinea
corporis (ringworm), tinea cruris (jock itch) and tinea pedis (athlete's foot).

0.34 fl oz (10 mL)

Dosage: 5-10 drops, once daily. Warning: If symptoms persist more than a few days,
contact a licensed practitioner. As with any drug, if you are pregnant or nursing a baby, seek
the advice of a health care professional before using this product. Keep this and all
medications out of the reach of children. In case of accidental overdose, seek
professional assistance or contact a Poison Control Center immediately. Protect from light
and heat. TAMPER EVIDENT: Do not use this product if tamper-evident seal on base of
bottle cap is missing or broken. INGREDIENTS: 10 mL Trichophyton verrucosum 6X in
a base of purified water.

Rev. 10/2010